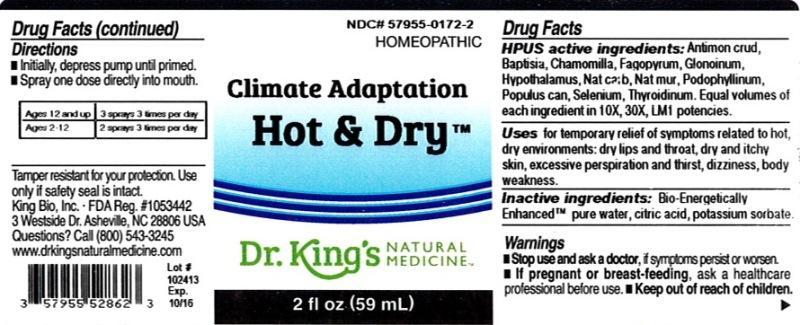 DRUG LABEL: Climate Adaptation Hot and Dry
NDC: 57955-0172 | Form: LIQUID
Manufacturer: King Bio Inc.
Category: homeopathic | Type: HUMAN OTC DRUG LABEL
Date: 20131115

ACTIVE INGREDIENTS: ANTIMONY TRISULFIDE 10 [hp_X]/59 mL; BAPTISIA TINCTORIA ROOT 10 [hp_X]/59 mL; MATRICARIA RECUTITA 10 [hp_X]/59 mL; FAGOPYRUM ESCULENTUM 10 [hp_X]/59 mL; NITROGLYCERIN 10 [hp_X]/59 mL; BOS TAURUS HYPOTHALAMUS 10 [hp_X]/59 mL; SODIUM CARBONATE 10 [hp_X]/59 mL; SODIUM CHLORIDE 10 [hp_X]/59 mL; PODOPHYLLUM RESIN 10 [hp_X]/59 mL; POPULUS BALSAMIFERA LEAF BUD 10 [hp_X]/59 mL; SELENIUM 10 [hp_X]/59 mL; THYROID, UNSPECIFIED 10 [hp_X]/59 mL
INACTIVE INGREDIENTS: WATER; CITRIC ACID MONOHYDRATE; POTASSIUM SORBATE

Climate Adaptation Hot and Dry™

ACTIVE INGREDIENT

Drug Facts__________________________________________________________________________________________________________

HPUS active ingredients: Antimonium crudum, Baptisia tinctoria, Chamomilla, Fagopyrum esculentum, Glonoinum, Hypothalamus, Natrum carbonicum, Natrum muriaticum, Podophyllinum, Populus candicans, Selenium metallicum, Thyroidinum. Equal volumes of each ingredient in 10X, 30X, LM1 potencies.

INDICATIONS AND USAGE

Uses for temporary relief of symptoms related to hot, dry environments: dry lips and throat, dry and itchy skin, excessive perspiration and thirst, dizziness, body weakness.

Inactive Ingredients:

Bio-Energetically Enhanced™ pure water, citric acid and potassium sorbate.

Warnings

Stop use and ask your doctor if symptoms persist or worsen.

If pregnant or breast-feeding, take only on advice of a healthcare professional.

Keep out of reach of children

DOSAGE AND ADMINISTRATION

- Initially, depress pump until primed.
- Spray one dose directly into mouth.
- Ages 12 and up- 3 sprays 3 times per day.
- Ages 2-12- 2 sprays 3 times per day.

OTHER SAFETY INFORMATION

Tamper resistant for your protection. Use only if safety seal is intact.

PURPOSE

Uses for temporary relief of symptoms related to hot, dry environments:

- dry lips and throat
- dry and itchy skin
- excessive perspiration and thirst
- dizziness
- body weakness